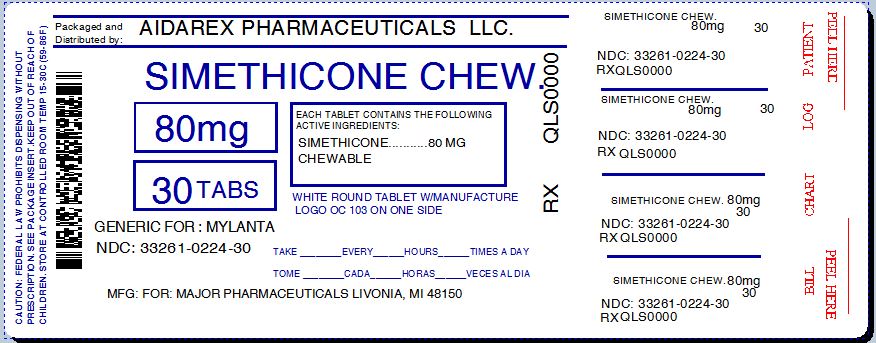 DRUG LABEL: Mi-Acid Gas Relief
NDC: 33261-224 | Form: TABLET, CHEWABLE
Manufacturer: Aidarex Pharmaceuticals LLC
Category: otc | Type: HUMAN OTC DRUG LABEL
Date: 20140203

ACTIVE INGREDIENTS: DIMETHICONE 80 mg/1 1
INACTIVE INGREDIENTS: SUCROSE; DEXTROSE; MAGNESIUM STEARATE; MALTODEXTRIN; CELLULOSE, MICROCRYSTALLINE; SORBITOL

Mi-Acid Gas Relief

Active ingredient (in each tablet)

Simethicone 80 mg

Purpose

Antigas

KEEP OUT OF REACH OF CHILDREN

Enter section text here

Uses

relieves:

- pressure
- bloating
- symptoms referred to as gas

Warnings

Keep out of reach of children. In case of overdose, get medical help or contact a poison control center immediately.

Directions

- chew 2 to 4 tablets thoroughly as needed after meals and at bedtime.
- do not exceed 6 tablets per day unless directed by a physician.

Other information

- do not use if inner seal is broken.
- store at room temperature
- avoid high humidity and excessive heat, above 40^0C (104^0F)

Inactive ingredients

compressible sugar, dextrose, flavor, magnesium stearate, maltodextrin, microcrystalline cellulose, sorbitol

Questions

To Report Adverse Drug Event Call: (800) 616-2471

PDP

Mi-Acid Gas Relief

Relieves Gas Pain, Pressure and Bloating

Simethicone 80 mg/Antiflatulent

30 Chewable Tablets